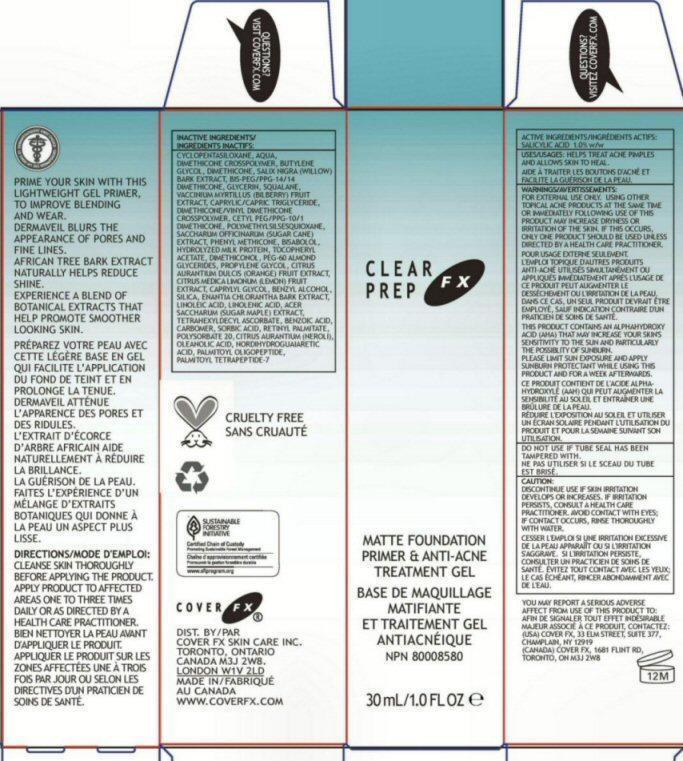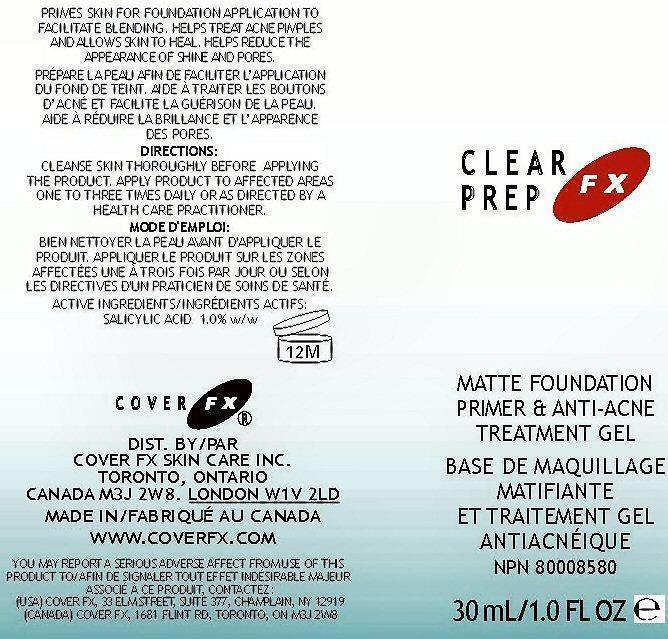 DRUG LABEL: ClearPrep FX
NDC: 68327-006 | Form: GEL
Manufacturer: Cover FX Skin Care, Inc.
Category: otc | Type: HUMAN OTC DRUG LABEL
Date: 20130219

ACTIVE INGREDIENTS: SALICYLIC ACID 1 g/100 mL
INACTIVE INGREDIENTS: CYCLOMETHICONE 5; WATER; DIMETHICONE/DIENE DIMETHICONE CROSSPOLYMER; BUTYLENE GLYCOL; DIMETHICONE; SALIX NIGRA BARK; GLYCERIN; SQUALANE; BILBERRY; MEDIUM-CHAIN TRIGLYCERIDES; DIMETHICONE/VINYL DIMETHICONE CROSSPOLYMER (SOFT PARTICLE); CETYL PEG/PPG-10/1 DIMETHICONE (HLB 5); POLYMETHYLSILSESQUIOXANE (4.5 MICRONS) ; SUGARCANE; PHENYL TRIMETHICONE; LEVOMENOL; CASEIN; ALPHA-TOCOPHEROL ACETATE; DIMETHICONOL (40 CST); PEG-60 ALMOND GLYCERIDES; PROPYLENE GLYCOL; ORANGE; LEMON; CAPRYLYL GLYCOL; BENZYL ALCOHOL; SILICON DIOXIDE; ANNICKIA CHLORANTHA BARK; LINOLEIC ACID; LINOLENIC ACID; ACER SACCHARUM BARK/SAP; TETRAHEXYLDECYL ASCORBATE; BENZOIC ACID; CARBOMER HOMOPOLYMER TYPE C (ALLYL PENTAERYTHRITOL CROSSLINKED) ; SORBIC ACID; VITAMIN A PALMITATE; POLYSORBATE 20; CITRUS AURANTIUM FLOWER OIL; OLEANOLIC ACID; MASOPROCOL; PALMITOYL OLIGOPEPTIDE; PALMITOYL TETRAPEPTIDE-7

Active Ingredients Section

SALICYLIC ACID 1%

Purpose Section

MATTE FOUNDATION PRIMER AND ANTI-ACNE TREATMENT GEL

Indications and Uses Section

USE: HELPS TREAT ACNE PIMPLES AND ALLOWS SKIN TO HEAL.

Warning Section

WARNINGS: FOR EXTERNAL USE ONLY. USING OTHER TOPICAL ACNE PRODUCTS AT THE SAME TIME OR IMMEDIATELY FOLLOWING USE OF THIS PRODUCT MAY INCREASE DRYNESS OR IRRITATION OF THE SKIN. IF THIS OCCURS, ONLY ONE PRODUCT SHOULD BE USED UNLESS DIRECTED BY A HEALTH CARE PRACTITIONER.

THIS PRODUCT CONTAINS AN ALPHAHYDROXY ACID (AHA) THAT MAY INCREASE YOUR SKINS SENSITIVITY TO THE SUN AND PARTICULARLY THE POSSIBILITY OF SUNBURN. PLEASE LIMIT SUN EXPOSURE AND APPLY SUNBURN PROTECTANT WHILE USING THIS PRODUCT AND FOR A WEEK AFTERWARDS.

DO NOT USE IF TUBE SEAL HAS BEEN TAMPERED WITH.

Caution Section

CAUTION: DISCONTINUE USE IF SKIN IRRITATION DEVELOPS OR INCREASES. IF IRRITATION PERSISTS, CONTACT A HEALTH CARE PRACTITIONER. AVOID CONTACT WITH THE EYES; IF CONTACT OCCURS, RINSE THOROUGHLY WITH WATER.

Report Adverse Section

YOU MAY REPORT A SERIOUS ADVERSE AFFECT FROM THIS PRODUCT TO (USA) COVER FX 33 ELM STREET, SUITE 377, CHAMPLAIN, NY 2919 (CANADA) COVER FX 1681 FLINT RD, TORONTO, ON M3J 2W8

Directions Section

PRIME YOUR SIN WITH THIS LIGHTWEIGHT GEL PRIMER, TO IMPROVE BLENDING AND WEAR. DERMAVEIL BLURS THE APPEARANCE OF PORES AND FINE LINES. AFRICAN TREE BARK EXTRACT NATURALLY HELPS REDUCE SHINE. EXPERIENCE A BLEND OF BOTANICAL EXTRACTS THAT HELP PROMOTE SMOOTHER LOOKING SKIN.

DIRECTIONS: CLEANSE SKIN THOROUGHLY BEFORE APPLYING THE PRODUCT. APPLY PRODUCT TO AFFECTED AREAS ONE TO THREE TIMES DAILY OR AS DIRECTED BY A HEALTH CARE PRACTITIONER.

Inactive Ingredient Section

INACTIVE INGREDIENTS: CYCLOPENTASILOXANE AQUA DIMETHICONE CROSSPOLYMER BUTYLENE GLYCOL DIMETHICONE SALIX NIGRA (WILLOW) BARK EXTRACT BIS-PEG/PPG-14/14 DIMETHICONE GLYCERIN SQUALANE VACCINIUM MYRTILLUS (BILBERRY) FRUIT EXTRACT CAPRYLIC/CAPRIC TRIGLYCERIDE DIMETHICONE/VINYL DIMETHICONE CROSSPOLYMER CETYL PEG/PPG-10/1 DIMETHICONE POLYMETHYLSILSESQUIOXANE SACCHARUM OFFICINARUM (SUGER CANE) EXTRACT PHENYL METHICONE BISABOLOL HYDROLYZED MILK PROTEIN TOCOPHERYL ACETATE DIMETHICONOL PEG-60 ALMOND GLYCERIDES PROPYLENE GLYCOL CITRUS AURANTIUM DULCIS (ORANGE) FRUIT EXTRACT CITRUS MEDICA LIMONUM (LEMON) FRUIT EXTRACT CAPRYLYL GLYCOL BENZYL ALCOHOL SILICA ENANTIA CHLORANTHA BARK EXTRACT LINOLEIC ACID LINOLENIC ACID ACER SACCHARUM (SUGAR MAPLE) EXTRACT TETRAHEXYLDECYL ASCORBATE BENZOIC ACID CARBOMER SORBIC ACID RETINYL PALMITATE POLYSORBATE 20 CITRUS AURANTIUM (NEROLI) OIL OLEANOLIC ACID NORDIHYDROGUAIARECTIC ACID PALMITOYL OLIGOPEPTIDE PALMITOYL TETRAPEPTIDE-7

Keep Out of Reach of Children Section

Enter section text here

Label Section

CLEARPREPFX MATTE FOUNDATION PRIMER AND ANTI-ACNE TREATMENT GEL

CRUELTY FREE SUSTAINABLE FORESTRY INITIATIVE CERTIFIED CHAIN OF CUSTODY WWW.SIFPROGRAM.ORG

COVER FX DIST. BY/PAR COVER FX SKIN CARE INC. TORONTO, ONTARIO CANADA M3J 2W8. LONDON W1V 2LD

DERMATOLOGISTS FIRST CHOICE